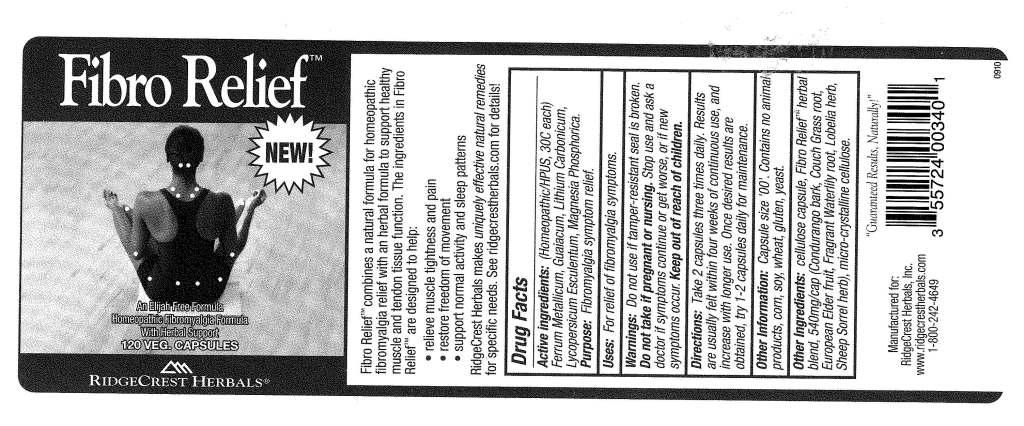 DRUG LABEL: Fibro Relief
NDC: 57520-0272 | Form: CAPSULE
Manufacturer: Apotheca Company
Category: homeopathic | Type: HUMAN OTC DRUG LABEL
Date: 20110420

ACTIVE INGREDIENTS: IRON 30 [hp_C]/1 1; GUAIACUM OFFICINALE RESIN 30 [hp_C]/1 1; LITHIUM CARBONATE 30 [hp_C]/1 1; TOMATO 30 [hp_C]/1 1; MAGNESIUM PHOSPHATE, DIBASIC TRIHYDRATE 30 [hp_C]/1 1
INACTIVE INGREDIENTS: CELLULOSE, MICROCRYSTALLINE; NYMPHAEA ODORATA ROOT; POWDERED CELLULOSE    ; MARSDENIA CONDURANGO BARK    ; ELYMUS REPENS ROOT    ; EUROPEAN ELDERBERRY    ; LOBELIA INFLATA    ; RUMEX CRISPUS ROOT

Fibro Relief

ACTIVE INGREDIENT

ACTIVE INGREDIENTS: Ferrum metallicum 30C, Guaiacum 30C, Lithium carbonicum 30C, Lycopersium esculentum 30C, Magnesia phosphorica 30C.

PURPOSE

USES: For relief of fibromyalgia symptoms.

WARNINGS

WARNINGS: Do not use if tamper-resistant seal is broken.

Do not take if pregnant or nursing.

Stop use and ask a doctor is symptoms continue or get worse, or if new symptoms occur.

Keep out of reach of children.

DOSAGE AND ADMINISTRATION

DIRECTIONS: Take 2 capsules three times daily. Results are usually felt within four weeks of continuous use, and increase with longer use. Once desired results are obtained, try 1-2 capsules daily for maintenance.

INACTIVE INGREDIENT

OTHER INGREDIENTS: Fragrant waterlily (root), Vegetable capsule, Condurango (bark), Couch grass (root), European elder (fruit), Sheep sorrel (herb), Lobelia (herb).

OTHER INFORMATION: Capsule size "00". Contains no animal products, corn, soy, wheat, gluten, yeast.

KEEP OUT OF REACH OF CHILDREN.

QUESTIONS

Manufactured for:

RidgeCrest Herbals, Inc.

www.ridgecrestherbals.com

1-800-242-4649

INDICATIONS AND USAGE

USES: For relief of fibromyalgia symptoms.

PACKAGE LABEL

Fibro Relief

NEW

An Elijah Free Formula

Homeopathic Fibromyalgia Formula

With Herbal Support

120 VEG CAPSULES

RIDGECREST HERBALS